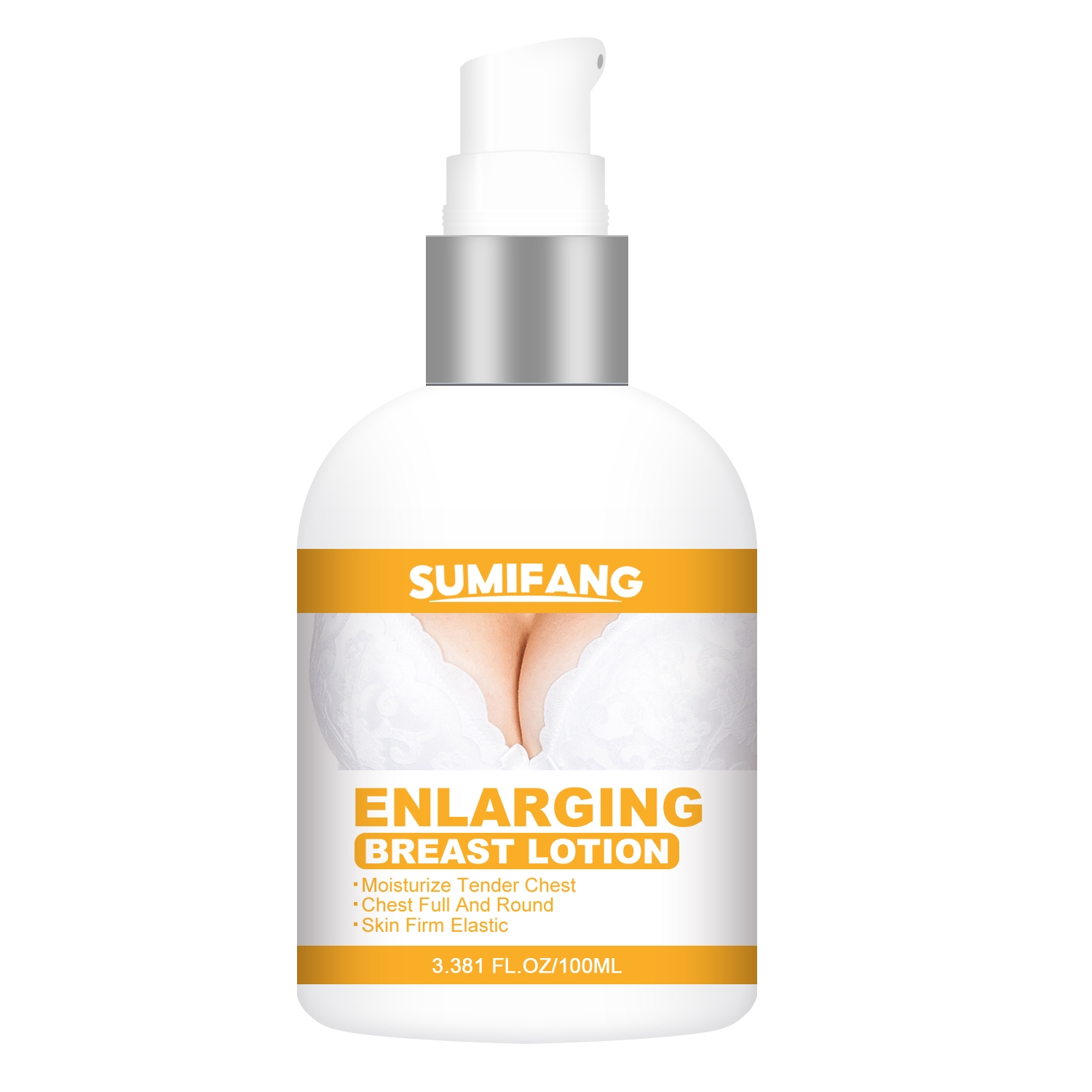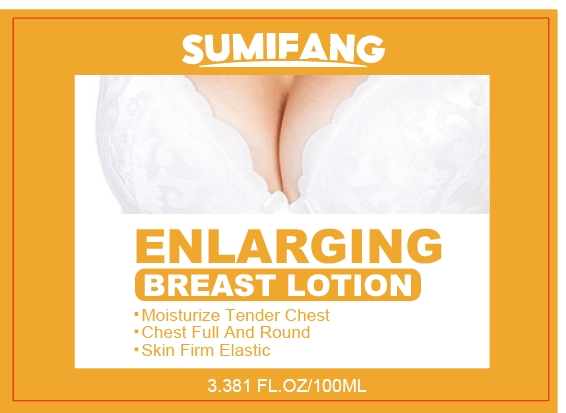 DRUG LABEL: ENLARGING BREASTLOTION
NDC: 84025-173 | Form: LOTION
Manufacturer: Guangzhou Yanxi Biotechnology Co.. Ltd
Category: otc | Type: HUMAN OTC DRUG LABEL
Date: 20240830

ACTIVE INGREDIENTS: GLYCERIN 5 mg/100 mL
INACTIVE INGREDIENTS: WATER

DOSAGE AND ADMINISTRATION

Massage lotion for breast skin massage

WARNINGS

keep out of children

INACTIVE INGREDIENT

AQUA

INDICATIONS AND USAGE

For daily breast skin care

keep out of children

PURPOSE

Moisturizes breast skin, tightens and smoothes skin